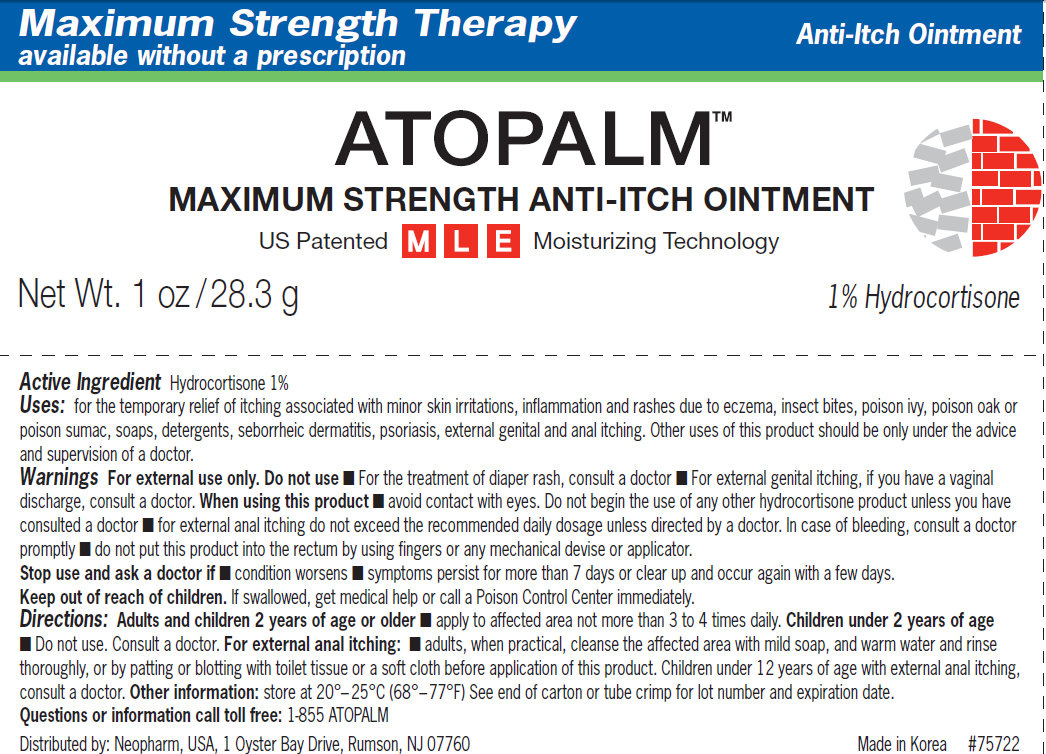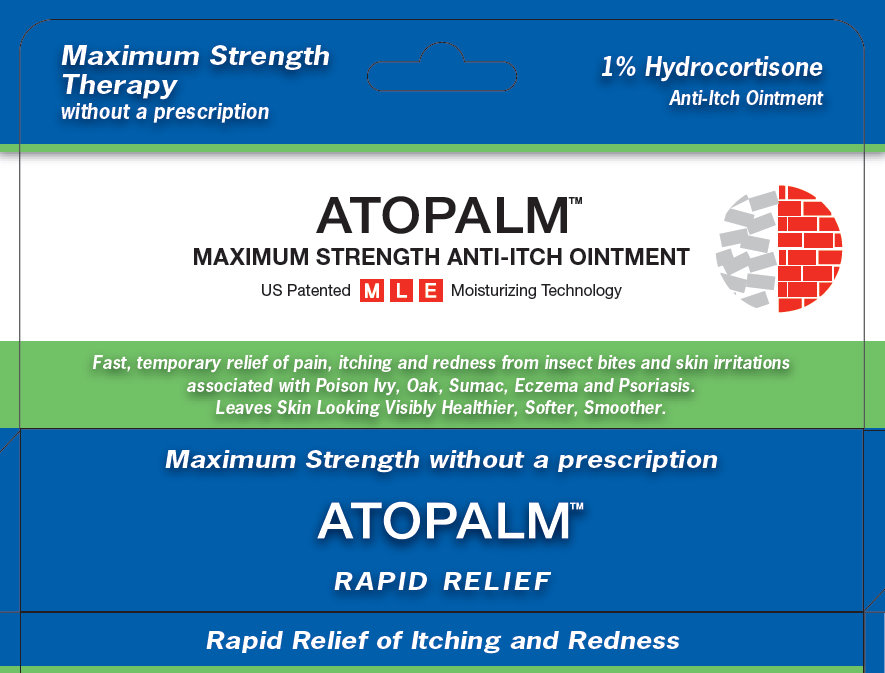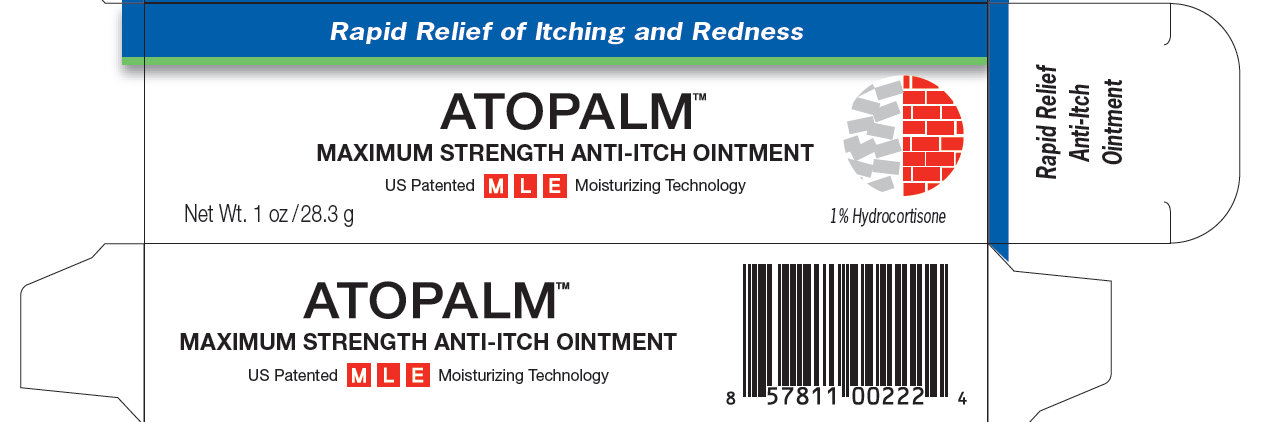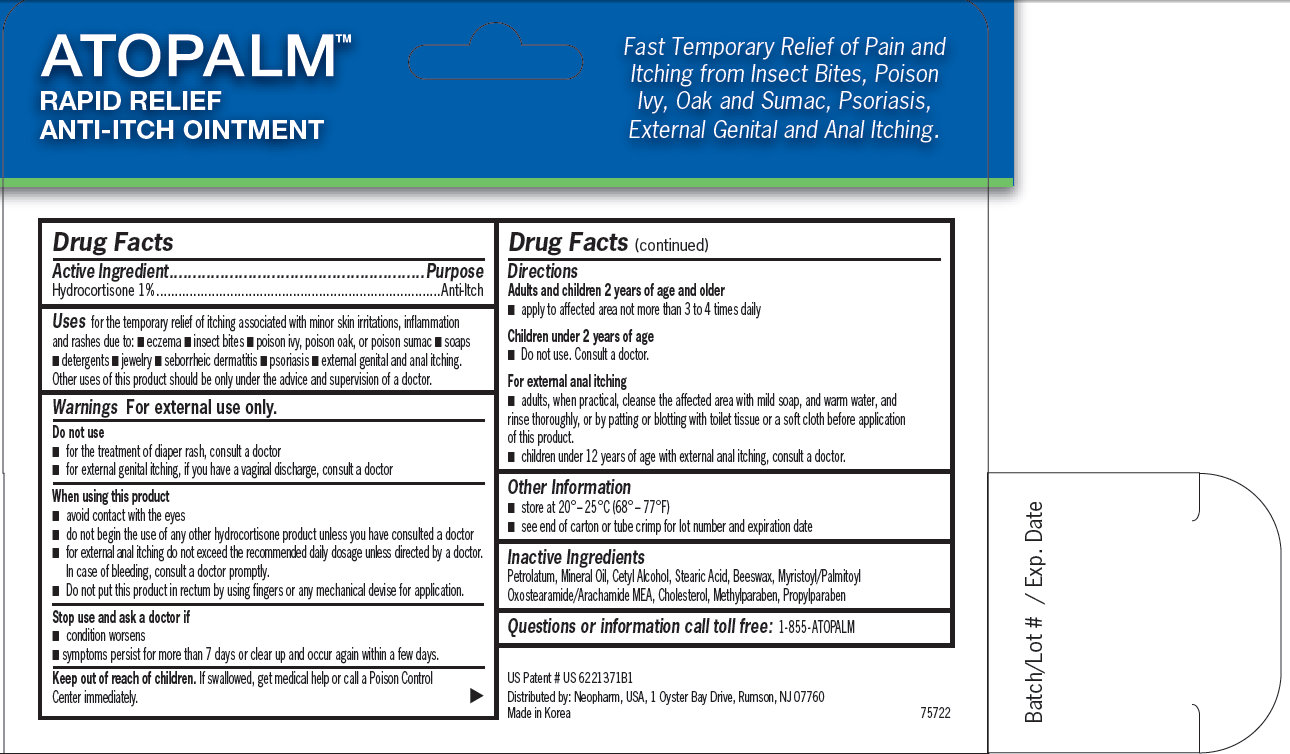 DRUG LABEL: Atopalm Maximum Strength Anti-Itch
                        
NDC: 51141-6010 | Form: OINTMENT
Manufacturer: NeoPharm Co., Ltd.
Category: otc | Type: HUMAN OTC DRUG LABEL
Date: 20111109

ACTIVE INGREDIENTS: HYDROCORTISONE 1 g/100 g
INACTIVE INGREDIENTS: PETROLATUM; MINERAL OIL; CETYL ALCOHOL; STEARIC ACID; YELLOW WAX; MYRISTOYL/PALMITOYL OXOSTEARAMIDE/ARACHAMIDE MEA; CHOLESTEROL; METHYLPARABEN; PROPYLPARABEN

Atopalm Maximum Strength Anti-Itch Ointment

Active Ingredient

Active Ingredient...........................Purpose
Hydrocortisone 1%.......................Anti-Itch

Uses

for the temporary relief of itching associated with minor skin irritations, inflammation and rashes due to: - eczema - insect bites - poison ivy, poison oak, or poison sumac - soaps - detergents - jewelry - seborrheic dermatitis - psoriasis - external genital and anal itching. Other uses of this product should be only under the advice and supervision of a doctor.

Warnings

For external use only.

Do not use

- for the treatment of diaper rash, consult a doctor - for external genital itching, if you have a vaginal discharge, consult a doctor

When using this product

- avoid contact with the eyes - do not begin the use of any other hydrocortisone product unless you have consulted a doctor - for external anal itching do not exceed the recommended daily dosage unless directed by a doctor. In case of bleeding, consult a doctor promptly. - Do not put this product in rectum by using fingers or any mechanical devise for application.

Stop use and ask a doctor if

- condition worsens - symptoms persist for more than 7 days or clear up and occur again within a few days.

Keep out of reach of children

Other Safety Information

If swallowed, get medical help or call a Poison Control Center immediately.

Directions

Adults and children 2 years of age and older - apply to affected area not more than 3 to 4 times daily Children under 2 years of age - Do not use. Consult a doctor. For external anal itching - adults, when practical, cleanse the affected area with mild soap, and warm water, and rinse thoroughly, or by patting or blotting with toilet tissue or a soft cloth before application of this product. - children under 12 years of age with external anal itching, consult a doctor.

Storage & Handling

- store at 20° – 25°C (68° – 77°F) - see end of carton or tube crimp for lot number and expiration date

Inactive Ingredients

Petrolatum, Mineral Oil, Cetyl Alcohol, Stearic Acid, Beeswax, Myristoyl/Palmitoyl Oxostearamide/Arachamide MEA, Cholesterol, Methylparaben, Propylparaben

Questions or information call toll free: 1-855- ATOPALM

Purpose

Anti-Itch

Description

US Patent # US 6221371B1 Distributed by: Neopharm, USA, 1 Oyster Bay Drive, Rumson, NJ 07760 Made in Korea Batch/Lot # / Exp. Date

PACKAGE LABEL

Maximum Strength Therapy available without a prescription Anti-Itch Ointment ATOPALM MAXIMUM STRENGTH ANTI-ITCH OINTMENT US Patented M L E Moisturizing Technology Net Wt. 1 oz /28.3 g 1% Hydrocortisone Active Ingredient Hydrocortisone 1% Uses: for the temporary relief of itching associated with minor skin irritations, inflammation and rashes due to eczema, insect bites, poison ivy, poison oak or poison sumac, soaps, detergents, seborrheic dermatitis, psoriasis, external genital and anal itching. Other uses of this product should be only under the advice and supervision of a doctor. Warnings For external use only. Do not use - For the treatment of diaper rash, consult a doctor - For external genital itching, if you have a vaginal discharge, consult a doctor. When using this product - avoid contact with eyes. Do not begin the use of any other hydrocortisone product unless you have consulted a doctor - for external anal itching do not exceed the recommended daily dosage unless directed by a doctor. In case of bleeding, consult a doctor promptly - do not put this product into the rectum by using fingers or any mechanical devise or applicator. Stop use and ask a doctor if - condition worsens - symptoms persist for more than 7 days or clear up and occur again with a few days. Keep out of reach of children. If swallowed, get medical help or call a Poison Control Center immediately. Directions: Adults and children 2 years of age or older - apply to affected area not more than 3 to 4 times daily. Children under 2 years of age - Do not use. Consult a doctor. For external anal itching: - adults, when practical, cleanse the affected area with mild soap, and warm water and rinse thoroughly, or by patting or blotting with toilet tissue or a soft cloth before application of this product. Children under 12 years of age with external anal itching, consult a doctor. Other information: store at 20° – 25°C (68° – 77°F) See end of carton or tube crimp for lot number and expiration date. Questions or information call toll free: 1-855 ATOPALM Distributed by: Neopharm, USA, 1 Oyster Bay Drive, Rumson, NJ 07760 Made in Korea #75722

PACKAGE LABEL

Maximum Strength Therapy without a prescription 1% Hydrocortisone Anti-Itch Ointment ATOPALM MAXIMUM STRENGTH ANTI-ITCH OINTMENT US Patented M L E Moisturizing Technology Fast, temporary relief of pain, itching and redness from insect bites and skin irritations associated with Poison Ivy, Oak, Sumac, Eczema and Psoriasis. Leaves Skin Looking Visibly Healthier, Softer, Smoother. Maximum Strength without a prescription ATOPALM RAPID RELIEF Rapid Relief of Itching and Redness

PACKAGE LABEL

Rapid Relief of Itching and Redness ATOPALM MAXIMUM STRENGTH ANTI-ITCH OINTMENT US Patented M L E Moisturizing Technology Net Wt. 1 oz /28.3 g 1% Hydrocortisone ATOPALM MAXIMUM STRENGTH ANTI-ITCH OINTMENT US Patented M L E Moisturizing Technology 8 57811 00222 4 Rapid Relief Anti-Itch Ointment

PACKAGE LABEL

ATOPALM RAPID RELIEF ANTI-ITCH OINTMENT Fast Temporary Relief of Pain and Itching from Insect Bites, Poison Ivy, Oak and Sumac, Psoriasis, External Genital and Anal Itching. US Patent # US 6221371B1 Distributed by: Neopharm, USA, 1 Oyster Bay Drive, Rumson, NJ 07760 Made in Korea 75722 Batch/Lot # / Exp. Date